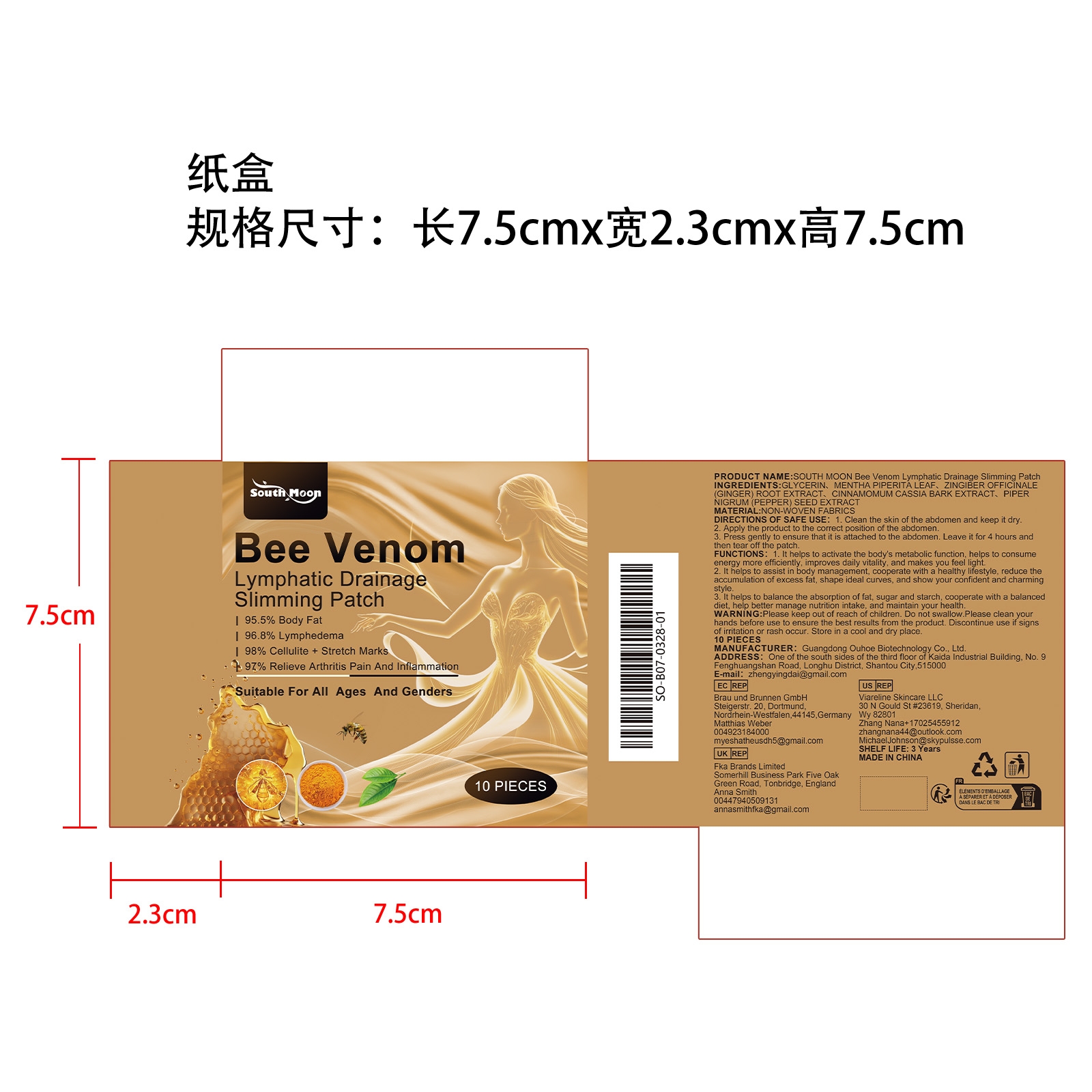 DRUG LABEL: SOUTH MOON Bee Venom Lymphatic Drainage Slimming Patch
NDC: 84744-050 | Form: PATCH
Manufacturer: Guangdong Ouhoe Biotechnology Co., Ltd.
Category: otc | Type: HUMAN OTC DRUG LABEL
Date: 20241021

ACTIVE INGREDIENTS: WHITE PEPPER 3 g/10 g; GINGER 1.5 g/10 g; CHINESE CINNAMON 1.5 g/10 g
INACTIVE INGREDIENTS: MENTHA PIPERITA LEAF 3 g/10 g; GLYCERIN 1 g/10 g

ACTIVE INGREDIENTS

WHITE PEPPER,GINGER,CHINESE CINNAMON

PURPOSE

1. It helps to activate the body's metabolic function, helps to consume energy more efficiently, improves daily vitality, and makes you feel light.2. It helps to assist in body management, cooperate with a healthy lifestyle, reduce the accumulation of excess fat, shape ideal curves, and show your confident and charming style.3. It helps to balance the absorption of fat, sugar and starch, cooperate with a balanced diet, help better manage nutrition intake, and maintain your health.

USE

1. Clean the skin of the abdomen and keep it dry.2. Apply the product to the correct position of the abdomen.3. Press gently to ensure that it is attached to the abdomen. Leave it for 4 hours and then tear off the patch.

WARNING

Please keep out of reach of children. Do not swallow.Please clean vourl hands before use to ensure the best results from the product. Discontinue use if signsl of irritation or rash occur. Store in a cool and dry place.

DO NOT USE

Discontinue use if signsl of irritation or rash occur.

STOP USE

Discontinue use if signsl of irritation or rash occur.

KEEP OUT OF REACH OF CHILDREN

Please keep out of reach of children. Do not swallow.

STORAGE AND HANDLING

Store in a cool and dry place.

INACTIVE INGREDIENT

GLYCERIN,MENTHA PIPERITA LEAF